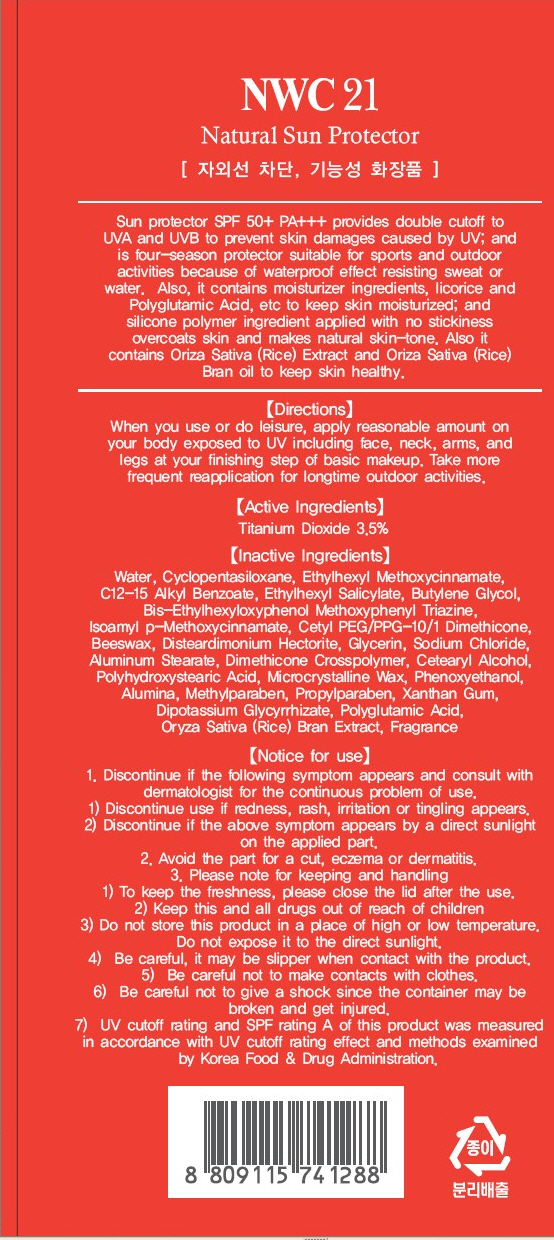 DRUG LABEL: NWC21 NATURAL SUN PROTECTOR
NDC: 45167-040 | Form: CREAM
Manufacturer: CLEANSIA CORPORATION LTD.
Category: otc | Type: HUMAN OTC DRUG LABEL
Date: 20100901

ACTIVE INGREDIENTS: TITANIUM DIOXIDE 2.10 mL/60 mL

Drug Facts

Active Ingredient: TITANIUM DIOXIDE

Inactive Ingredients:
Water, Cyclopentasiloxane, Ethylhexyl Methoxycinnamate, C12-15 Alkyl Benzoate, Ethylhexyl Salicylate, Butylene Glycol, Bis-Ethylhexyloxyphenol Methoxyphenyl Triazine,
Isoamyl p-Methoxycinnamate, Cetyl PEG/PPG-10/1 Dimethicone, Beeswax, Disteardimonium Hectorite, Glycerin, Sodium Chloride, Aluminum Stearate, Dimethicone Crosspolymer, Cetearyl Alcohol, Polyhydroxystearic Acid, Microcrystalline Wax, Phenoxyethanol, Alumina, Methylparaben, Propylparaben, Xanthan Gum, Dipotassium Glycyrrhizate, Polyglutamic Acid, Oryza Sativa (Rice) Bran Extract, Fragrance

Directions:
When you use or do leisure, apply reasonable amount on your body exposed to UV including face, neck, arms, and legs at your finishing step of basic makeup.
Take more frequent reapplication for longtime outdoor activities.
Notice for use:
1. Discontinue if the following symptom appears and consult with dermatologist for the continuos problem of use.
1) Discontinue use if redness, rash, irritation or tingling appears.
2) Discontinue if the above symptom appears by a direct sunlight on the applied part.
2. Avoid the part for a cut, eczema or dermatitis.
3. Please note for keeping and handling.
1) To keep the freshness, please close the lid after the use.
2) Keep this and all drugs out of reach of children.
3) Do not store this product in a place of high or low temperature. Do not expose it to the direct sunlight.
4) Be careful, it may be slipper when contact with the product.
5) Be careful not to make contacts with clothes.
6) Be careful not to give a shock since the container may be broken and get injured.
7) UV cutoff rating and SPF rating A of this product was measured in accordance with UV cutoff rating effect and methods examined by Korea Food and Drug Administration.